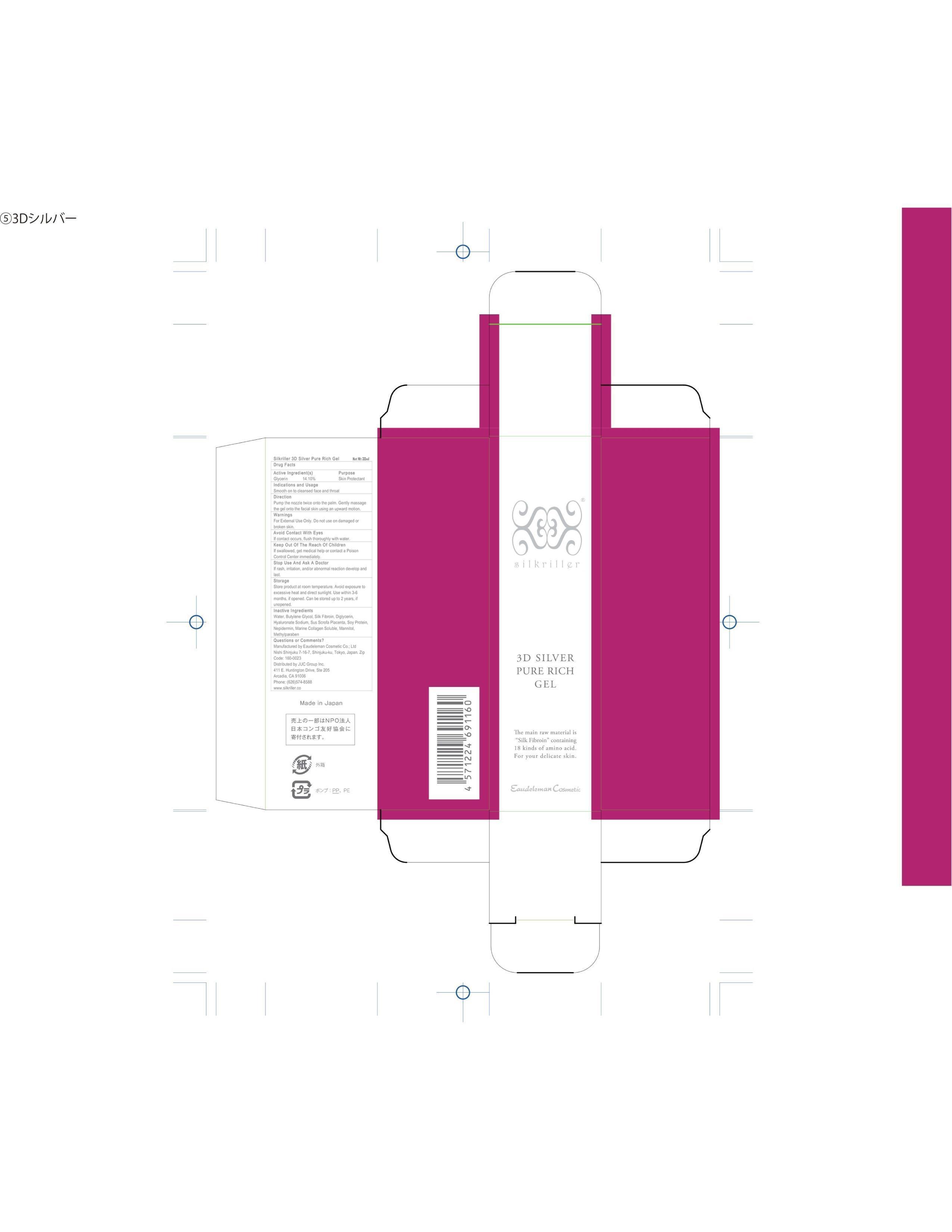 DRUG LABEL: Silkriller 3D Silver Pure Rich Gel
NDC: 69893-101 | Form: GEL
Manufacturer: Eaudleman Cosmetic Co Ltd
Category: otc | Type: HUMAN OTC DRUG LABEL
Date: 20151104

ACTIVE INGREDIENTS: GLYCERIN 13.8 mg/100 mL
INACTIVE INGREDIENTS: WATER; BUTYLENE GLYCOL; SILK FIBROIN; DIGLYCERIN; HYALURONATE SODIUM; SUS SCROFA PLACENTA; SOY PROTEIN; NEPIDERMIN; MARINE COLLAGEN, SOLUBLE; MANNITOL; METHYLPARABEN

Eaudleman Cosmetic Co.; Ltd

Active Ingredient

Glycerin 14.10%

Purpose

Glycerin - Skin Protectant

Indications and Usage

Smooth on to cleansed face and throat.

Directions

Pump the nozzle twice on the palm. Gently massage the gel onto the facial skin using an upward motion.

Warnings

For External Use Only. Do not use on damaged or broken skin.

Keep out of reach of children.

If swallowed, get medical help or contact a Poison Control Center immediately.

Avoid Contact With Eyes.

If contact occurs, flush thoroughly with water.

Stop Use and Ask a Doctor If

Rash, irritation and/or abnormal reaction develop and last.

Storage

Store product at room temperature. Avoid exposure to excessive heat and direct sunlight. Use within 3-6 months if opened. Can be stored up to 2 years if unopened.

Questions or Comments?

Manufactured by Eaudeleman Cosmetic Co.; Ltd

Nishi Shinjuku 7-16-7, Shinjuku-ku, Tokyo, Japan 160-0023

Distributed by JUC Group Inc.

411 E. Huntington Drive, Suite 205

Arcadia, CA 91006

Phone: (626)574-8588

www.silkriller.co

Inactive Ingredients

WATER, BUTYLENE GLYCOL, SILK FIBROIN, DIGLYCERIN, HYALURONATE SODIUM, SUS CROFA PLACENTA, SOY PROTEIN, NEPIDERMIN, MARINE COLLAGEN SOLUBLE, MANNITOL, METHYLPARABEN